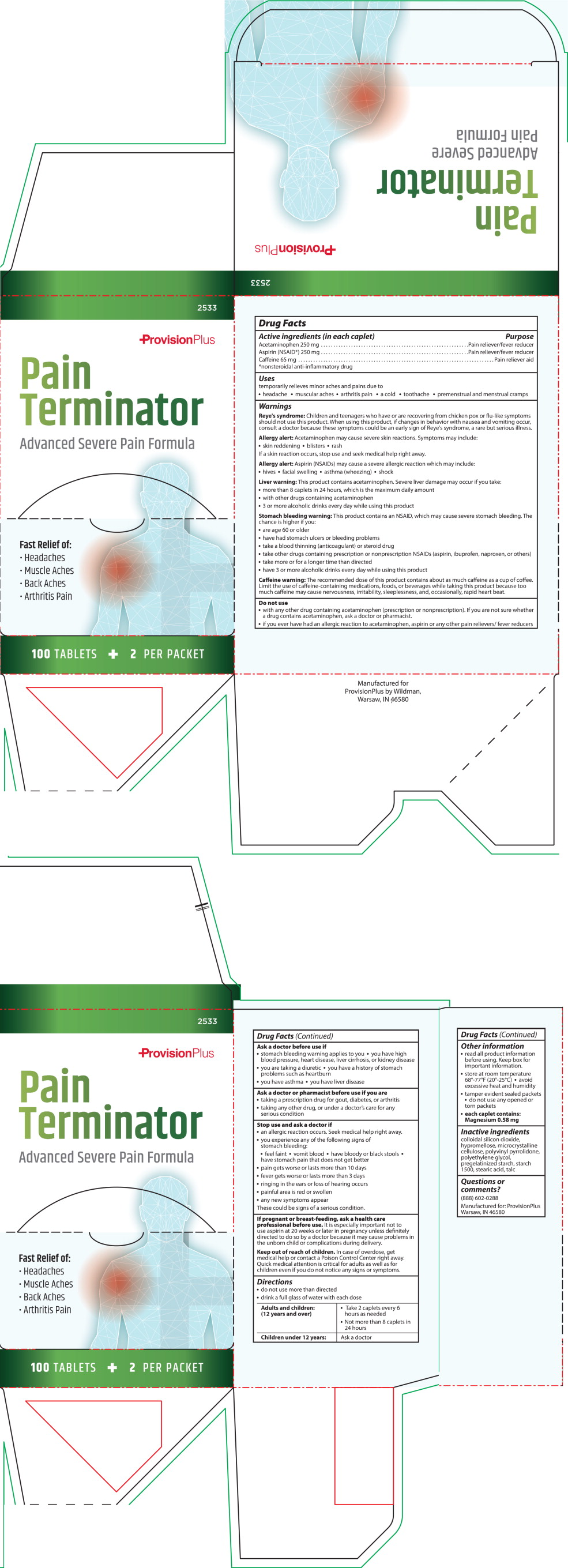 DRUG LABEL: Pain Terminator 
NDC: 84269-2533 | Form: CAPSULE
Manufacturer: Wildman Business Group
Category: otc | Type: HUMAN OTC DRUG LABEL
Date: 20260112

ACTIVE INGREDIENTS: CAFFEINE 65 mg/1 1; ACETAMINOPHEN 250 mg/1 1; ASPIRIN 250 mg/1 1
INACTIVE INGREDIENTS: SILICON DIOXIDE; TALC; HYPROMELLOSE, UNSPECIFIED; MICROCRYSTALLINE CELLULOSE; POLYETHYLENE GLYCOL, UNSPECIFIED; STARCH, CORN; STEARIC ACID; POVIDONE, UNSPECIFIED

ACTIVE INGREDIENT

Active ingredients (in each caplet)

Acetaminophen 250 mg

Aspirin (NSAID*) 250 mg

Caffeine 65 mg

*nonsteroidal anti-inflammatory drug

PURPOSE

Pain reliever/fever reducer

Pain reliever/fever reducer

Pain reliever aid

INDICATIONS & USAGE

Uses

temporarily relieves minor aches and pains due to

- headache
- muscular aches
- arthritis pain
- a cold
- toothache
- premenstrual and menstrual cramps

WARNINGS

Reye's syndrome: Children and teenagers who have or are recovering from chicken pox or flu-like symptoms should not use this product. When using this product, if changes in behavior with nausea and vomiting occur, consult a doctor because these symptoms could be an early sign of Reye's syndrome, a rare but serious illness.

Allergy alert: Acetaminophen may cause severe skin reactions. Symptoms may include:

- skin reddening
- blisters
- rash

If a skin reaction occurs, stop use and seek medical help right away.

Allergy alert: Aspirin (NSAIDs) may cause a severe allergic reaction which may include:

- hives
- facial swelling
- asthma (wheezing)
- shock

Liver warning: This product contains acetaminophen. Severe liver damage may occur if you take:

- more than 8 caplets in 24 hours, which is the maximum daily amount
- with other drugs containing acetaminophen
- 3 or more alcoholic drinks every day while using this product

Stomach bleeding warning: This product contains an NSAID, which may cause severe stomach bleeding. The chance is higher if you:

- are age 60 or older
- have had stomach ulcers or bleeding problems
- take a blood thinning (anticoagulant) or steroid drug
- take other drugs containing prescription or nonprescription NSAIDs (aspirin, ibuprofen, naproxen, or others)
- take more or for a longer time than directed
- have 3 or more alcoholic drinks every day while using this product

Caffeine warning: The recommended dose of this product contains about as much caffeine as a cup of coffee. Limit the use of caffeine-containing medications, foods, or beverages while taking this product because too much caffeine may cause nervousness, irritability, sleeplessness, and, occasionally, rapid heart beat

DO NOT USE

- with any other drug containing acetaminophen (prescription or nonprescription). If you are not sure whether a drug contains acetaminophen, ask a doctor or pharmacist.
- if you ever have had an allergic reaction to acetaminophen, aspirin or any other pain relievers/ fever reducers

ASK DOCTOR

Ask a doctor before use if

- stomach bleeding warning applies to you
- you have high blood pressure, heart disease, liver cirrhosis, or kidney disease
- you are taking a diuretic
- you have a history of stomach problems such as heartburn
- you have asthma
- you have liver disease

ASK DOCTOR/PHARMACIST

Ask a doctor or pharmacist before use if you are

- taking a prescription drug for gout, diabetes, or arthritis
- taking any other drug, or under a doctor's care for any serious condition

STOP USE

Stop use and ask a doctor if

- an allergic reaction occurs. Seek medical help right away.
- you experience any of the following signs of stomach bleeding:
- feel faint
- vomit blood
- have bloody or black stools
- have stomach pain that does not get better
- pain gets worse or lasts more than 10 days
- fever gets worse or lasts more than 3 days
- ringing in the ears or loss of hearing occurs
- painful area is red or swollen
- any new symptoms appear

These could be signs of a serious condition.

PREGNANCY OR BREAST FEEDING

If pregnant or breast-feeding, ask a health professional before use. It is especially important not to use aspirin at 20 weeks or later in pregnancy unless definitely directed to do so by a doctor because it may cause problems in the unborn child or complications during delivery.

Keep out of reach of children. In case of overdose, get medical help or contact a Poison Control Center

right away. Quick medical attention is critical for adults as well as for children even if you do not notice any signs or symptoms.

DOSAGE & ADMINISTRATION

Directions

- do not use more than directed
- drink a full glass of water with each dose

Adults and children: (12 years and over) Take 2 caplets every 6 hours as needed; not more than 8 caplets in 24 hours

Children under 12 years: Ask a doctor

OTHER SAFETY INFORMATION

Other information

- read all product information before using. Keep box for important information.
- store at room temperature 68º-77ºF (20º-25ºC)
- avoid excessive heat and humidity
- tamper evident sealed packets
- do not use any opened or torn packets
- each caplet contains: Magnesium 0.58 mg

INACTIVE INGREDIENT

Inactive ingredients

colloidal silicon dioxide, hypromellose, microcrystalline cellulose, polyvinyl pyrrolidone, polyethylene glycol, pregelatinized starch, starch 1500, stearic acid, talc

QUESTIONS

Questions or comments? (888) 602-0288

Principal Display Panel – 100 Caplet Box Label

2533

ProvisionPlus

PAIN TERMINATOR

Advanced Severe Pain Formula

Fast Relief of:

- Headaches
- Muscle Aches
- Back Aches
- Arthritis Pain

100 Tablets

2 Per Packet